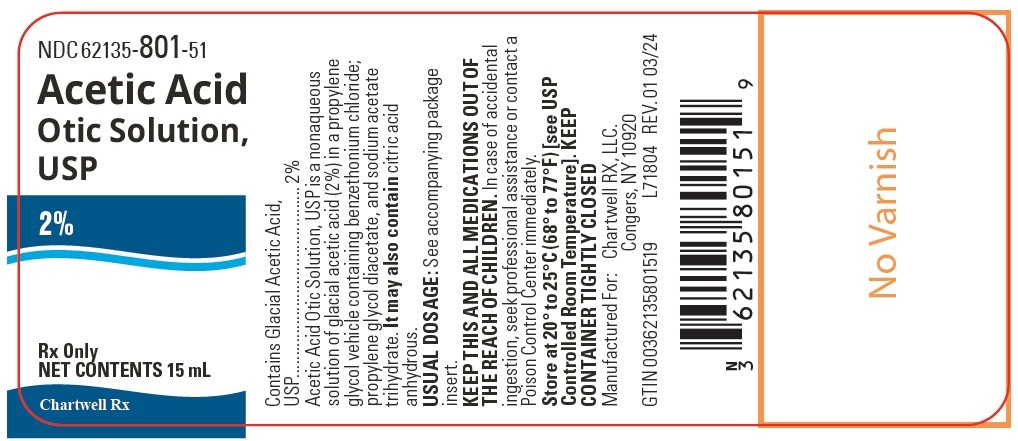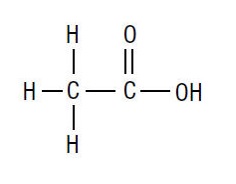 DRUG LABEL: ACETIC ACID
NDC: 62135-801 | Form: SOLUTION
Manufacturer: Chartwell RX, LLC
Category: prescription | Type: HUMAN PRESCRIPTION DRUG LABEL
Date: 20240326

ACTIVE INGREDIENTS: ACETIC ACID 20 mg/1 mL
INACTIVE INGREDIENTS: PROPYLENE GLYCOL; BENZETHONIUM CHLORIDE; PROPYLENE GLYCOL DIACETATE; SODIUM ACETATE; ANHYDROUS CITRIC ACID

ACETIC ACID OTIC SOLUTION, USP

DESCRIPTION

Acetic Acid Otic Solution, USP is a colorless to pale yellow color nonaqueous solution of glacial acetic acid (2%), in a propylene glycol vehicle containing benzethonium chloride, propylene glycol diacetate, and sodium acetate trihydrate. It may also containcitric acid anhydrous.

The molecular formula for acetic acid is CH3COOH, with a molecular weight of 60.05. The structural formula is:

Acetic Acid Otic Solution, USP is available as a nonaqueous otic solution buffered at pH 3 for use in the external ear canal.

CLINICAL PHARMACOLOGY

Acetic acid is anti-bacterial and anti-fungal; propylene glycol is hydrophilic and provides a low surface tension; benzethonium chloride is a surface active agent that promotes contact of the solution with tissues.

INDICATIONS AND USAGE

For the treatment of superficial infections of the external auditory canal caused by organisms susceptible to the action of the antimicrobial.

CONTRAINDICATIONS

Hypersensitivity to acetic acid otic solution or any of the ingredients. Perforated tympanic membrane is considered a contraindication to the use of any medication in the external ear canal.

WARNINGS

Discontinue promptly if sensitization or irritation occurs.

PRECAUTIONS

Transient stinging or burning may be noted occasionally when the solution is first instilled into the acutely inflamed ear.

Pediatric Use

Safety and Effectiveness in pediatric patients below the age of 3 years have not been established.

ADVERSE REACTIONS

Stinging or burning may be noted occasionally; local irritation has occurred very rarely.

DOSAGE AND ADMINISTRATION

Carefully remove all cerumen and debris to allow acetic acid otic solution to contact infected surfaces directly. To promote continuous contact, insert a wick of cotton saturated with the solution into the ear canal; the wick may also be saturated after insertion. Instruct the patient to keep the wick in for at least 24 hours and to keep it moist by adding 3 to 5 drops of the solution every 4 to 6 hours. The wick may be removed after 24 hours but the patient should continue to instill 5 drops of acetic acid otic solution 3 or 4 times daily thereafter, for as long as indicated. In pediatric patients, 3 to 4 drops may be sufficient due to the smaller capacity of the ear canal.

HOW SUPPLIED

Acetic Acid Otic Solution, USP, 2% is a colorless to pale yellow color solution supplied in 15 mL bottle with dropper plug and extended TIP closure.

They are available as follows:

Bottle of 15 mL – NDC 62135-801-51

RECOMMENDED STORAGE

Store at 20° to 25°C (68° to 77°F) [see USP Controlled Room Temperature].

KEEP CONTAINER TIGHTLY CLOSED

Rx Only

Manufactured for:

Chartwell RX, LLC.

Congers, NY 10920

L71805

Rev: 03/2024

PRINCIPAL DISPLAY PANEL

Acetic Acid Otic Solution, USP 2% - NDC 62135-801-51 - 15 mL Bottle Label